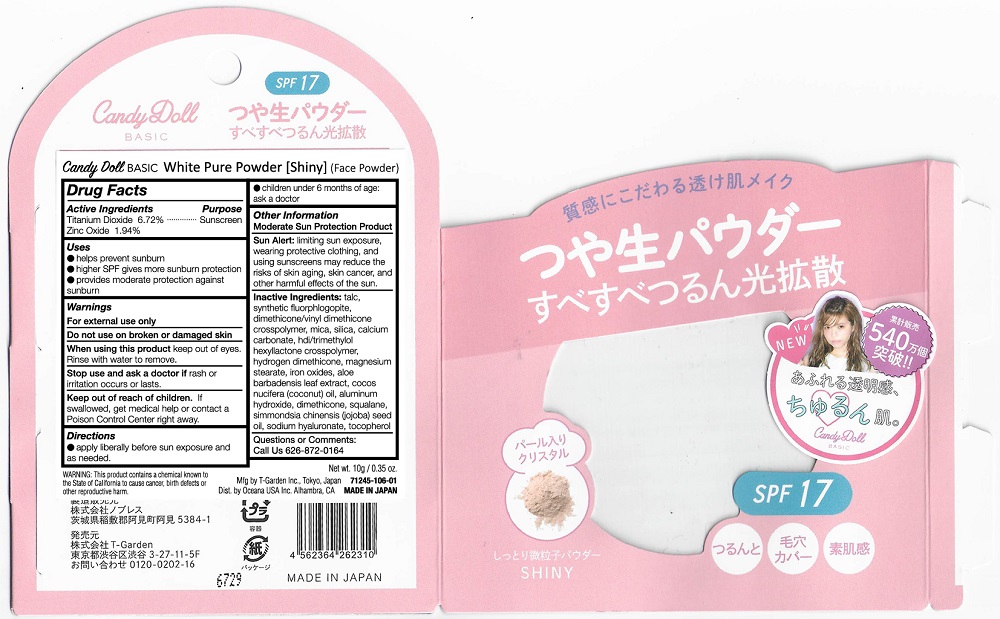 DRUG LABEL: Candy Doll White Pure Powder Shiny
NDC: 71245-106 | Form: POWDER
Manufacturer: T-Garden Inc
Category: otc | Type: HUMAN OTC DRUG LABEL
Date: 20170215

ACTIVE INGREDIENTS: ZINC OXIDE 0.194 g/10 g; TITANIUM DIOXIDE 0.672 g/10 g
INACTIVE INGREDIENTS: SQUALANE; DIMETHICONE/VINYL DIMETHICONE CROSSPOLYMER (SOFT PARTICLE); TALC; BROWN IRON OXIDE; COCONUT OIL

Candy Doll Pure White Powder Shiny

Active Ingredients

Titanium Dioxide 6.72%

Zinc Oxide 1.94%

Purpose

Sunscreen

Warnings

For external use only

Do not use on broken or damaged skin

When Using

When using this product keep out of eyes. Rinse with water to remove.

Stop use and ask a doctor if rash or irritation occurs or lasts.

Keep Out of Reach of Children

Directions

apply liberally before sun exposure and as needed

children under 6 months of age: ask a doctor

Inactive Ingredients

talc, synthetic flourphlogopite, dimethicone/vinyl dimethicone crosspolymer, mica, silica, calcium carbonate, hdi/trimethylol hexyllactone crosspolymer, magnesium stearate, hydrogen dimethicone, iron oxides, aloe barbadensis leaf extract, cocos nucifera (coconut) oil, aluminum hydroxide, dimethicone, squalene, simmondsia chinensis (jojoba) seed oil, sodium hyaluronate, tocopherol

Questions

Questions or Comments: Call Us 626-872-0164

PDP Image

CandyDoll White Pure Powder Shiny.jpg